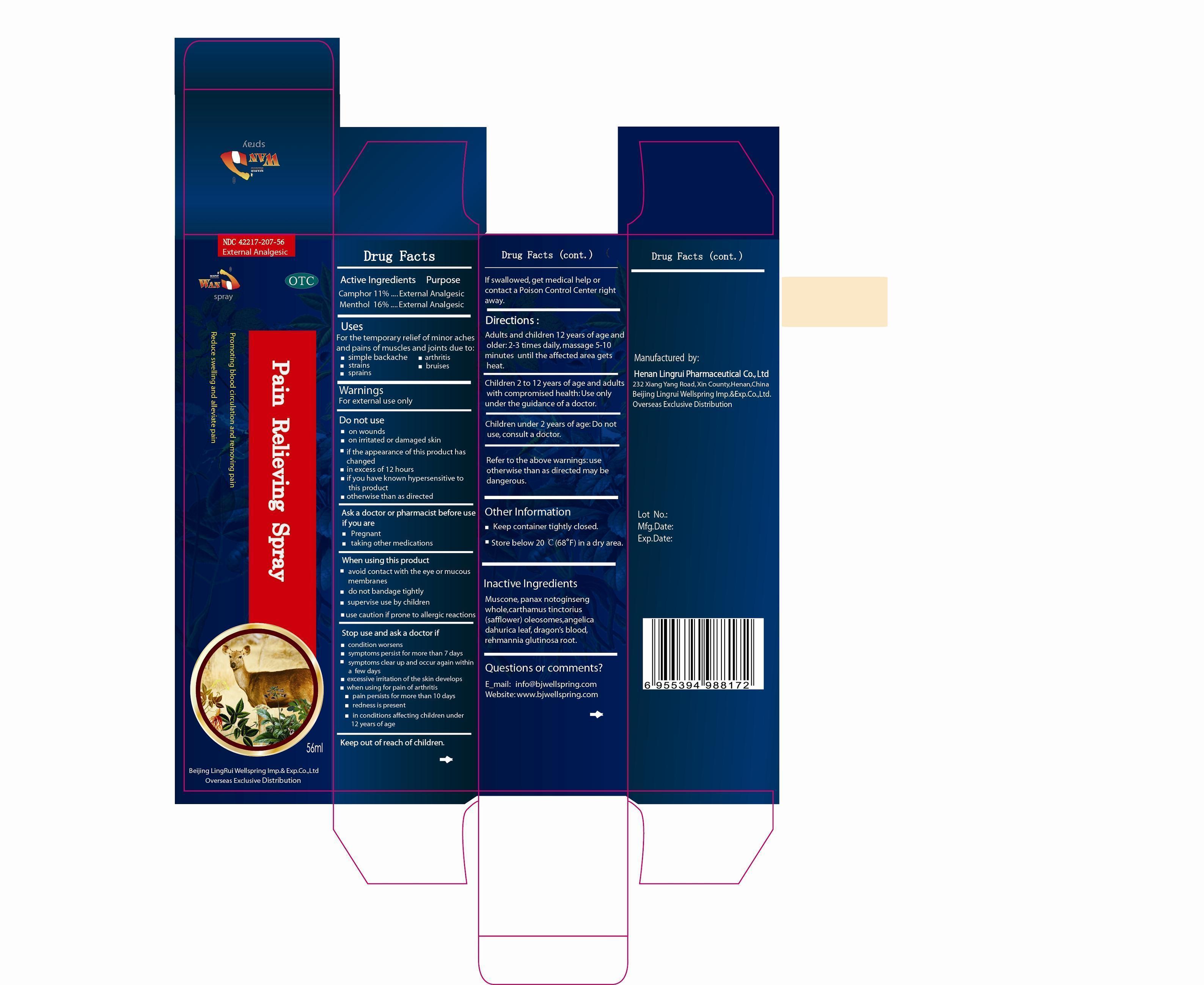 DRUG LABEL: Pain Relieving
NDC: 42217-207 | Form: SPRAY
Manufacturer: Henan Lingrui Pharmaceutical Co Ltd
Category: otc | Type: HUMAN OTC DRUG LABEL
Date: 20150319

ACTIVE INGREDIENTS: CAMPHOR (SYNTHETIC) 11 g/100 mL; MENTHOL 16 g/100 mL
INACTIVE INGREDIENTS: MUSCONE; PANAX NOTOGINSENG WHOLE; CARTHAMUS TINCTORIUS (SAFFLOWER) OLEOSOMES; ANGELICA DAHURICA LEAF; DRAGON'S BLOOD; REHMANNIA GLUTINOSA ROOT

Henan Lingrui Pharmaceutical Co Ltd

Active Ingredients

Camphor 11%
Menthol 16%

Purpose

Camphor External Analgesic

Menthol External Analgesic

Uses

For the temporary relief of minor aches and pains of muscles and joints due to:

simple backache

arthritis

strains

bruises

sprains

Warnings

For External Use Only.

Do not use

on wounds

on irritated or damaged skin

if the appearance of this product has changed

in excess of 12 hours

if you have known hypersensitive to this product

otherwise than as directed

ASK A DOCTOR OR PHARMACIST BEFORE USE IF YOU ARE

pregnant

taking other medications

WHEN USING THIS PRODUCT

avoid contact with the eye or mucous membranes

do not bandage tightly

supervise use by children

use caution if prone to allergic reactions

STOP USE AND ASK A DOCTOR IF

condition worsens

symptoms persist for more than 7 days

symptoms clear up and occur again within a few days

excessive irritation of the skin develops

when using for pain of arthritis

pain persists for more than 10 days

redness is present

in conditions affecting children under 12 years of age

Keep out of reach of children.

If swallowed, get medical help or contact a Poison Control Center right away.

Directions

Adults and children 12 years of age and older: two or three times daily, massage 5-10 minutes until the affected area gets heat.

Children 2 to 12 years of age and adults with compromised health: Use only under the guidance of a doctor.
Children under 2 years of age: Do not use, consult a doctor.
Refer to the above warnings: use otherwise than as directed may be dangerous.

Other Information

Keep container tightly closed.

Store below 20 ℃ (68 ℉) in a dry area.

Inactive Ingredients

MUSCONE, PANAX NOTOGINSENG WHOLE, CARTHAMUS TINCTORIUS (SAFFLOWER) OLEOSOMES, ANGELICA DAHURICA LEAF, DRAGON'S BLOOD, REHMANNIA GLUTINOSA ROOT

Questions or Comments?

E-mail: info@bjwellspring.com

Website: www.bjspringwell.com

Manufactured by

Henan Lingrui Pharmaceutical Co. Ltd.

232 Xiang Yang Road, Xin County, Henan, China

Beijing Lingrui Wellspring Imp. & Exp. Co.; Ltd.

Overseas Exclusive Distribution